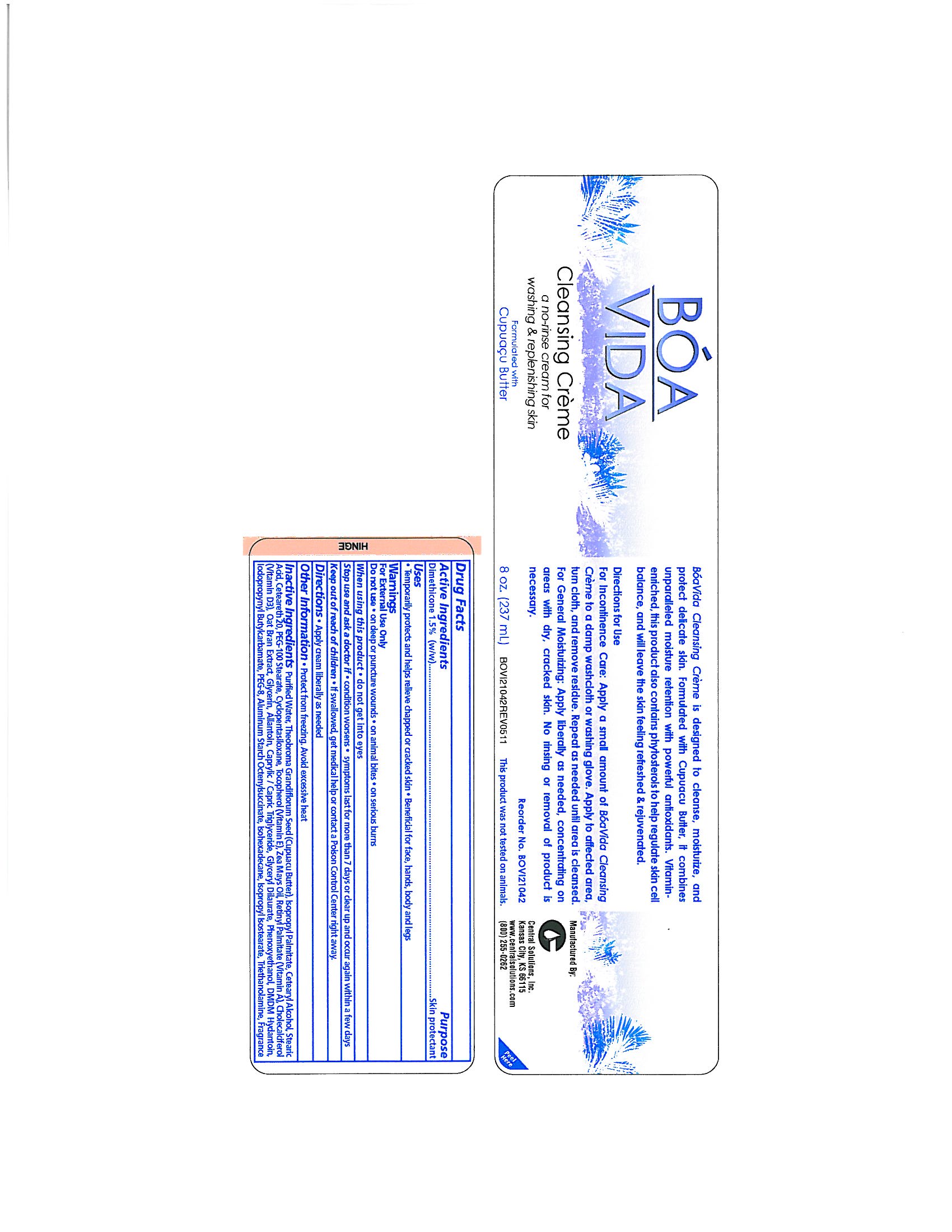 DRUG LABEL: BOA VIDA Cleansing
NDC: 62654-146 | Form: CREAM
Manufacturer: Central Solutions Inc
Category: otc | Type: HUMAN OTC DRUG LABEL
Date: 20241209

ACTIVE INGREDIENTS: DIMETHICONE 1.5 g/100 mL
INACTIVE INGREDIENTS: WATER; THEOBROMA GRANDIFLORUM SEED; ISOPROPYL PALMITATE; CETOSTEARYL ALCOHOL; STEARIC ACID; POLYOXYL 20 CETOSTEARYL ETHER; PEG-100 STEARATE; CYCLOMETHICONE 5; TOCOPHEROL; CORN OIL; VITAMIN A PALMITATE; CHOLECALCIFEROL; OAT BRAN; GLYCERIN; ALLANTOIN; PHENOXYETHANOL; DMDM HYDANTOIN; IODOPROPYNYL BUTYLCARBAMATE; POLYETHYLENE GLYCOL 400; ALUMINUM STARCH OCTENYLSUCCINATE; ISOHEXADECANE; TROLAMINE

Drug Facts 62654-146

Active Ingredients

Dimethicone 1.5% (w/w)

Purpose

Skin protectant

Uses

Temporarily protects and helps relieve chapped or cracked skin

Beneficial for face, hands, body and legs

Warnings

For External Use Only

Do not use

on deep or puncture wounds

on animal bites

on serious burns

When using this product

do not get in eyes

Stop use and ask a doctor if

condition worsens

symptoms last for more than 7 days or clear up and occur again within a few days

Keep out of reach of children

If swallowed, get medical help or contact a Poison Control Center right away.

Directions

Apply cream liberally as needed

Other Information

Protect from freezing.

Avoid excessive heat

Inactive Ingredients

Purified Water, Theobroma Grandiflorum Seed (Cupuacu Butter), Isopropyl Palmitate, Cetearyl Alcohol, Stearic Acid, Ceteareth 20, PEG-100 Stearate, Cyclopentasiloxane, Tocopherol (Vitamin E), Zea Mays Oil, Retinyl Palmitate (Vitamin A), Cholecalciferol (Vitamin D3), Oat Bran Extract, Glycerin, Allantoin, Caprylic/Capric Triglyceride, Glyceryl Dilaurate, Phenoxyethanol, DMDM Hydantoin, Iodopropynyl Butylcarbamate, PEG-8, Aluminum Starch Octenylsuccinate, Isohexadecane, Isopropyl Isostearate, Triethanolamine, Fragrance

PACKAGE LABEL

BOA

VIDA

Cleansing Creme

a no-rinse cream for

washing and replenishing skin

Formulated with

Cupuacu Butter

8 oz. (237 mL)